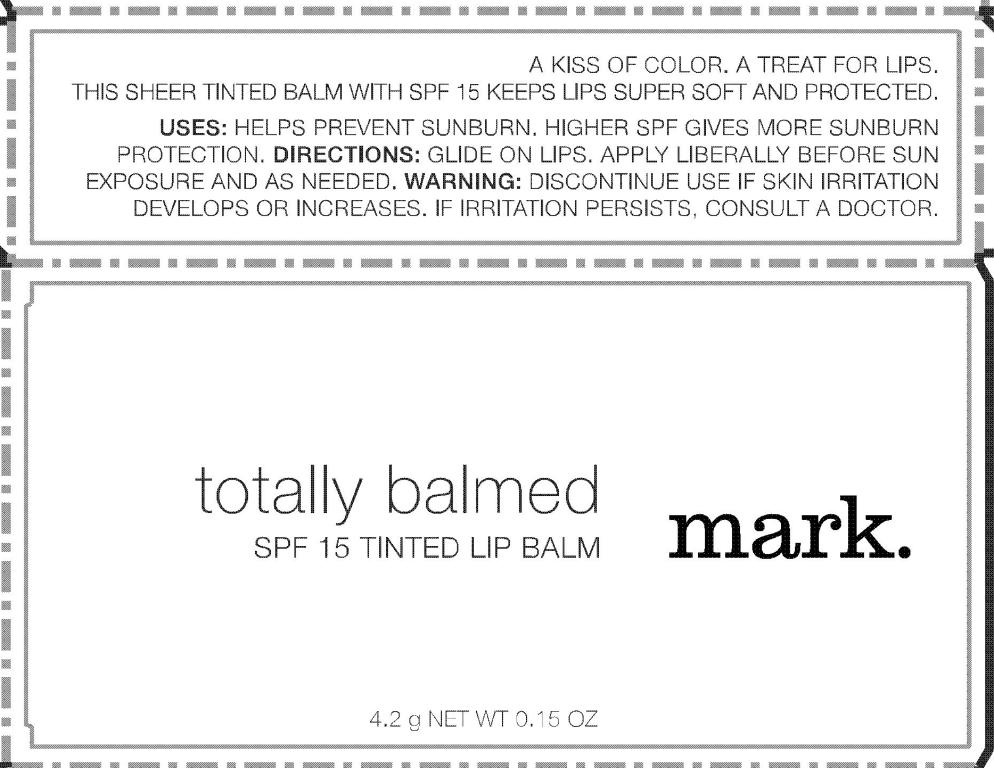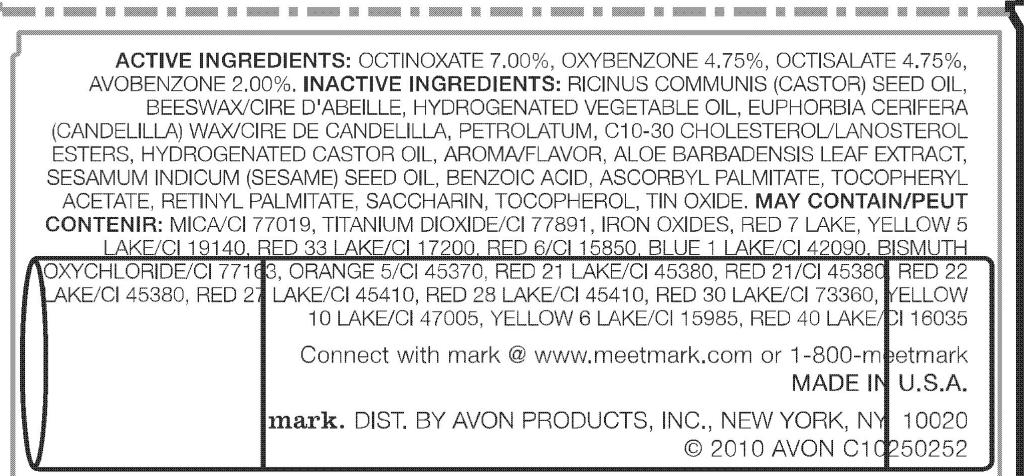 DRUG LABEL: mark
NDC: 10096-0201 | Form: LIPSTICK
Manufacturer: Avon Products, Inc.
Category: otc | Type: HUMAN OTC DRUG LABEL
Date: 20100602

ACTIVE INGREDIENTS: OCTINOXATE 294 mg/4.2 g; OXYBENZONE 199.5 mg/4.2 g; OCTISALATE 199.5 mg/4.2 g; AVOBENZONE  84 mg/4.2 g
INACTIVE INGREDIENTS: PETROLATUM; HYDROGENATED CASTOR OIL; BENZOIC ACID; ASCORBYL PALMITATE; SACCHARIN; MICA; TITANIUM DIOXIDE; BISMUTH OXYCHLORIDE

INDICATIONS AND USAGE

Uses: Helps prevent sunburn. Higher SPF gives more sunburn protection.

DOSAGE AND ADMINISTRATION

Directions: Glide on lips. Apply liberally before sun
exposure and as needed.

WARNINGS

Warning: Discontinue use if skin irritation develops or increases. If irritation persists, consult a doctor.

Active Ingredients:
OCTINOXATE 7.00%
OXYBENZONE 4.75%
OCTISALATE 4.75%
AVOBENZONE 2.00%

INACTIVE INGREDIENT

RICINUS COMMUNIS (CASTOR) SEED OIL
BEESWAX/CIRE D'ABEILLE
HYDROGENATED VEGETABLE OIL
EUPHORBIA CERIFERA (CANDELILLA) WAX/CIRE DE CANDELILLA
PETROLATUM
C10-30 CHOLESTEROL/LANOSTEROL ESTERS
HYDROGENATED CASTOR OIL
AROMA/FLAVOR
ALOE BARBADENSIS LEAF EXTRACT
SESAMUM INDICUM (SESAME) SEED OIL
BENZOIC ACID
ASCORBYL PALMITATE
TOCOPHERYL ACETATE
RETINYL PALMITATE
SACCHARIN
TOCOPHEROL
TIN OXIDE
MAY CONTAIN:
MICA/CI 77019
TITANIUM DIOXIDE/CI 77891
IRON OXIDES
RED 7 LAKE
YELLOW 5 LAKE/CI 19140
RED 33 LAKE/CI 17200
RED 6/CI 15850
BLUE 1 LAKE/CI 42090
BISMUTH OXYCHLORIDE/CI 77163
ORANGE 5/CI 45370
RED 21 LAKE/CI 45380
RED 21/CI 45380
RED 22 LAKE/CI 45380
RED 27 LAKE/CI 45410
RED 28 LAKE/CI 45410
RED 30 LAKE/CI 73360
YELLOW 10 LAKE/CI 47005
YELLOW 6 LAKE/CI 15985
RED 40 LAKE/CI 16035